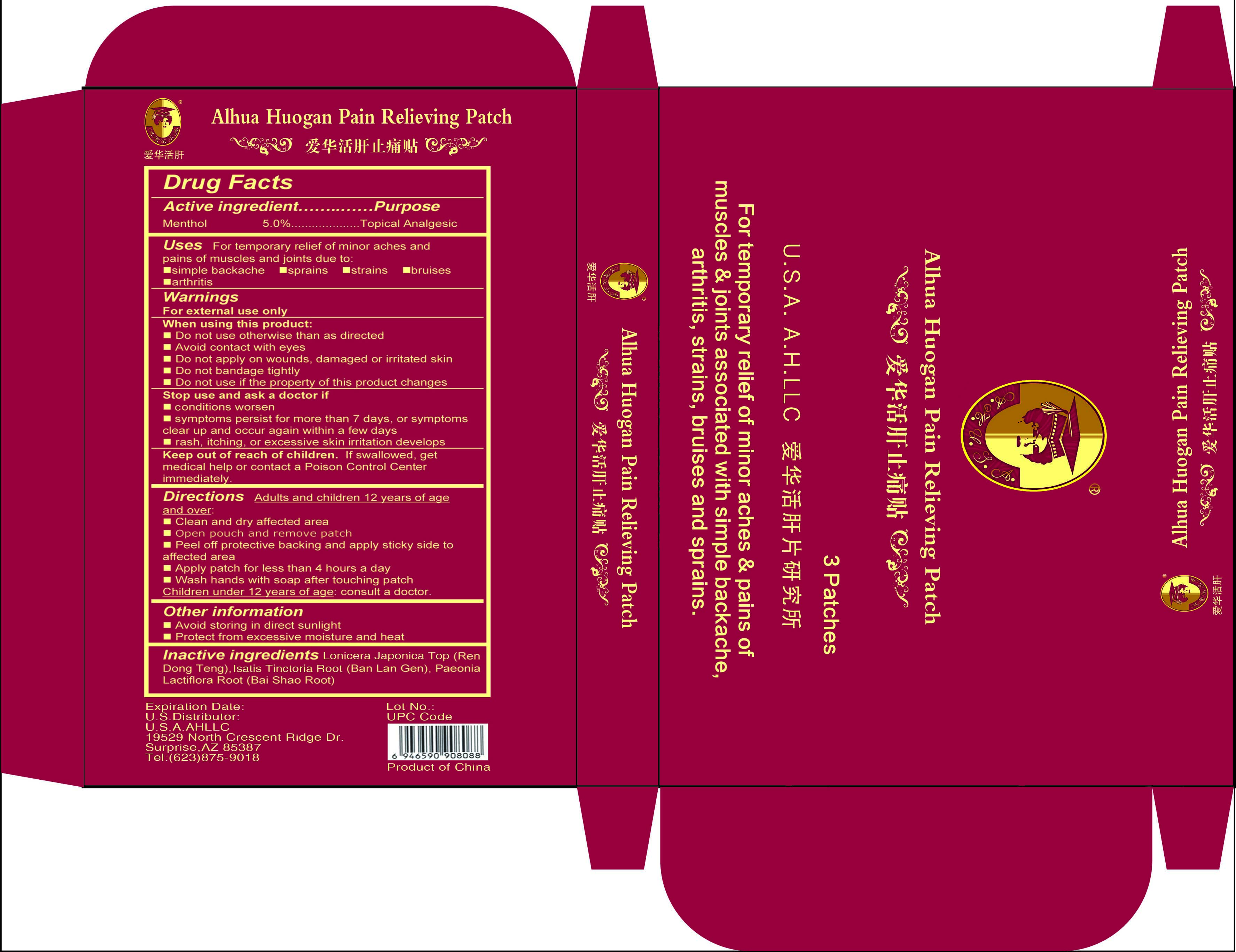 DRUG LABEL: Alhua Huogan Pain Relieving Patch
NDC: 53791-118 | Form: PATCH
Manufacturer: U.S.A. AH LLC
Category: otc | Type: HUMAN OTC DRUG LABEL
Date: 20130205

ACTIVE INGREDIENTS: Menthol 30 mg/1 1
INACTIVE INGREDIENTS: LONICERA JAPONICA TOP; ISATIS TINCTORIA ROOT; PAEONIA LACTIFLORA ROOT

Drug Facts

Active Ingredient

Menthol 5%

Purpose

Topical Analgesic

Uses

For temporary relief of minor aches and pains of muscles and joints due to:

- simple backache
- sprains
- strains
- bruises
- arthritis

Warnings

For external use only

When using this product

- Do not use otherwise than as directed
- Avoid contact with eyes
- Do not apply on wounds, damaged or irritated skin
- Do not bandage tightly
- Do not use if the property of this product changes

Stop use and ask a doctor if

- Conditions worsen
- Symptoms persist for more than 7 days, or symptoms clear up and occur again within a few days
- Rash, itching, or excessive skin irritation develops

Keep out of reach of children.

If swallowed, get medical help or contact a Poison Control Center immediately.

Directions

Adults and children 12 years of age and over:

- Clean and dry affected area
- Open pouch and remove patch
- Peel off protective backing and apply sticky side to affected area
- Apply patch for less than 4 hours a day
- Wash hands with soap after touching patch

Children under 12 years of age: consult a doctor.

Other information

- Avoid storing in direct sunlight
- Protect from excessive moisture and heat

Inactive ingredients

Honeysuckle Vine (Ren Dong Teng), Isatis Tinctoria (Ban Lan Gen), Paeonia Lactiflora Root (Bai Shao Root)

Carton Label Image

Carton label imagecartonlabel